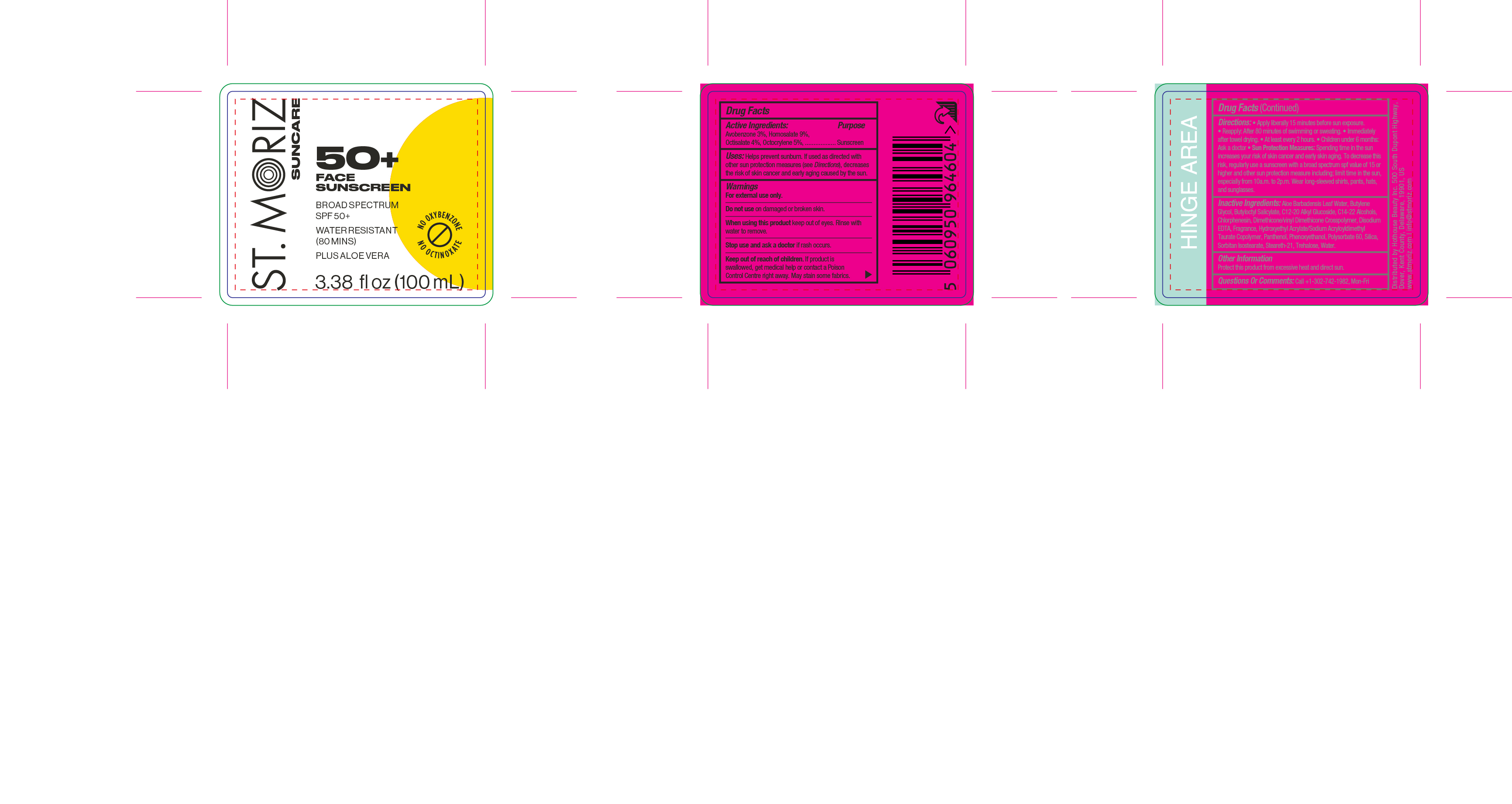 DRUG LABEL: St. Moriz Suncare 50 Face Sunscreen
NDC: 85178-2325 | Form: LOTION
Manufacturer: Hothouse Beauty Inc
Category: otc | Type: HUMAN OTC DRUG LABEL
Date: 20250120

ACTIVE INGREDIENTS: OCTISALATE 40 mg/1 mL; HOMOSALATE 90 mg/1 mL; OCTOCRYLENE 50 mg/1 mL; AVOBENZONE 30 mg/1 mL
INACTIVE INGREDIENTS: HYDROXYETHYL ACRYLATE/SODIUM ACRYLOYLDIMETHYL TAURATE COPOLYMER (45000 MPA.S AT 1%); ALOE BARBADENSIS LEAF WATER; BUTYLENE GLYCOL; POLYSORBATE 60; SILICA; PHENOXYETHANOL; WATER; EDETATE DISODIUM; CHLORPHENESIN; BUTYLOCTYL SALICYLATE; DIMETHICONE/VINYL DIMETHICONE CROSSPOLYMER (SOFT PARTICLE); TREHALOSE; STEARETH-21; JOJOBA OIL; C12-20 ALKYL GLUCOSIDE; C14-22 ALCOHOLS; PANTHENOL; SORBITAN ISOSTEARATE

St. Moriz Suncare 50+ Face Sunscreen SPF 50

Active Ingredient

Active Ingredients:

homosalate 9%
octocrylene 5%
octisalate 4%
avobenzone 3%

Uses

- Helps prevent sunburn
- If used as directed with other sun protection measures (see Directions) decreases risk of skin cancer and early skin aging caused by the sun

Warnings

- For external use only.
- Do not use on damaged or broken skin
- When using this product [bullet] keep out of eyes. Rinse with water to remove.
- Stop use and ask a doctor if [bullet] rash or irritation develops and lasts.
- Keep out of reach of children, If product is swallowed, get medical help or contact poison control centre right away.
- To ensure compatibility, we recommend patch testing before first use. In the unlikely event of a negative reaction, discontinue use and consult your medical practitioner.

Do not use on damaged or broken skin

When using this product

keep out of eyes. Rinse with water to remove.

Keep out of reach of children. If product is swallowed, get medical help or contact Poison Control Center right away.

Directions

- Apply generously 15 minutes before sun exposure”
- Reapply [bullet] after 80 minutes of swimming or sweating [bullet] immediately after towel drying [bullet] at least every 2 hours
- Children under 6 months of age: Ask a doctor
- Sun Protection Measures.Spending time in the sun increases your risk of skin cancer and early skin aging. To decrease this risk, regularly use a sunscreen with a Broad Spectrum SPF value of 15 or higher and other sun protection measures including:  limit time in the sun, especially from 10 a.m. - 2 p.m.  wear long-sleeved shirts, pants, hats, and sunglasses

Inactive ingredients

Aloe Barbadensis Leaf Water, Butylene Glycol, Butyloctyl Salicylate, C12-20 Alkyl Glucoside, C14-22 Alcohols, Chlorphenesin, Dimethicone/vinyl Dimethicone Crosspolymer, disodium edta, Fragrance, Hydroxyethyl Acrylate/Sodium Acryloyldimethyl Taurate Copolymer, Panthenol, Phenoxyethanol, Polysorbate 60, Silica, Sorbitan Isostearate
Steareth-21, Trehalose, Water

Other Information

Protect the product in this container from excessive heat and direct sun. Store below 30 degrees celcius.

Uses

Helps prevent sunburn.

St. Moriz Suncare 50+ Face Sunscreen

NDC 85178-2325-1

100 mL / 3.38 fl oz

Principal Display Panel and information panel primary container: